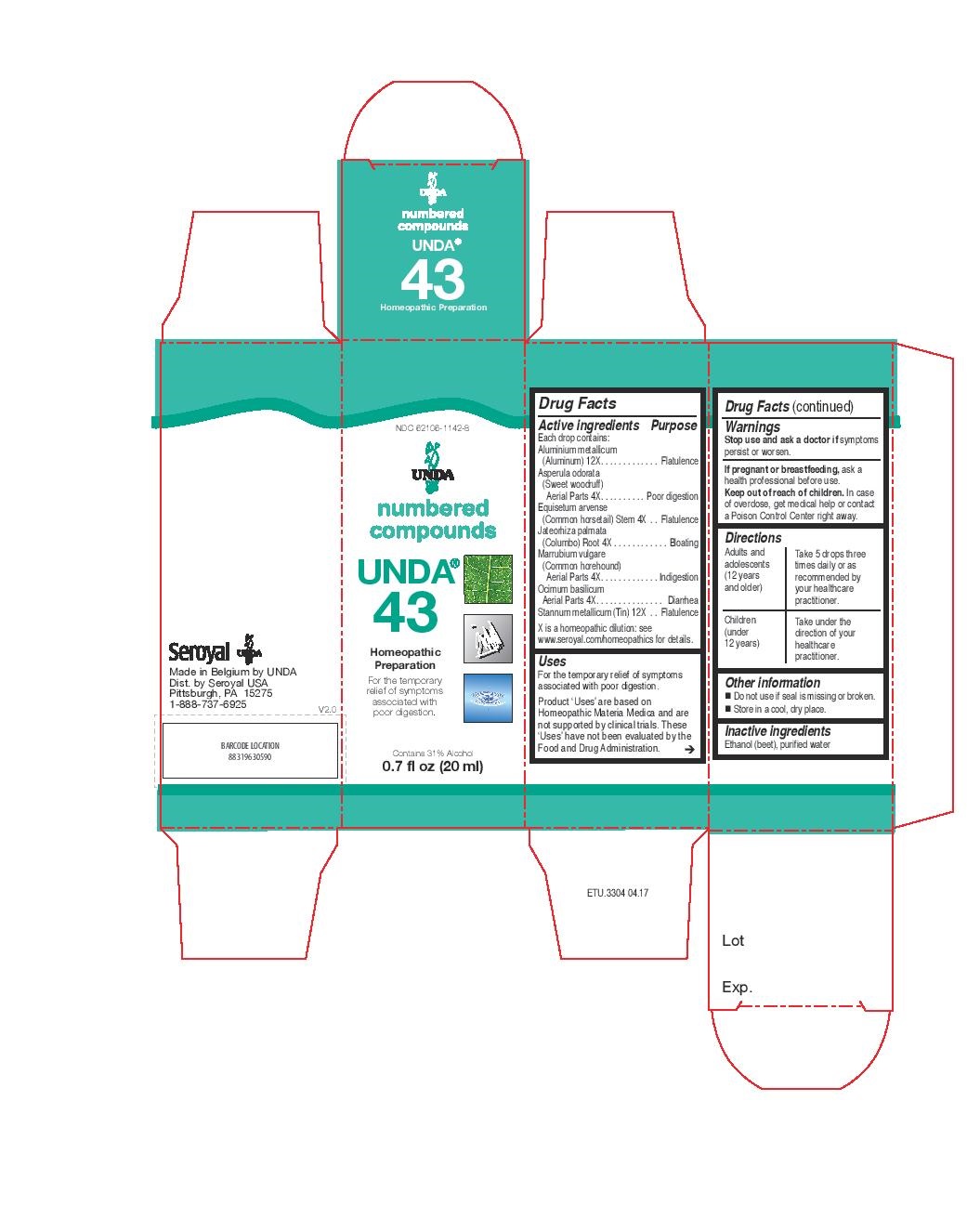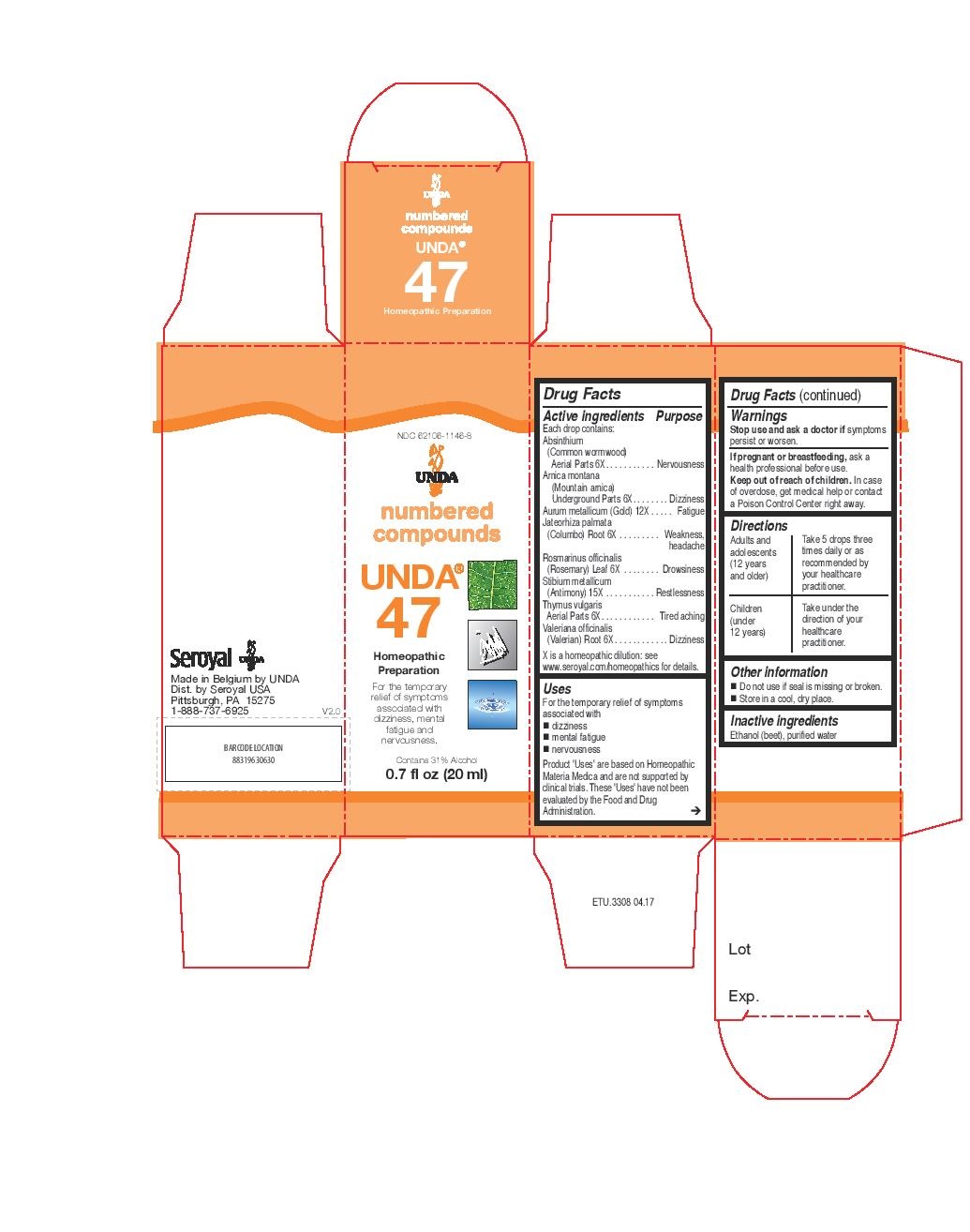 DRUG LABEL: UNDA 43
NDC: 62106-1142 | Form: LIQUID
Manufacturer: Seroyal USA
Category: homeopathic | Type: HUMAN OTC DRUG LABEL
Date: 20221109

ACTIVE INGREDIENTS: EQUISETUM ARVENSE TOP 4 [hp_X]/20 mL; JATEORHIZA CALUMBA ROOT 4 [hp_X]/20 mL; GALIUM ODORATUM 4 [hp_X]/20 mL; MARRUBIUM VULGARE 4 [hp_X]/20 mL; BASIL 4 [hp_X]/20 mL; TIN 12 [hp_X]/20 mL; ALUMINUM 12 [hp_X]/20 mL
INACTIVE INGREDIENTS: ALCOHOL; WATER

UNDA 43 and 47

Active ingredients

Each drop contains:

Absinthium (Common wormwood) Aerial Parts 6X
Arnica montana (Mountain arnica) Underground Parts 6X
Aurum metallicum (Gold) 12X
Jateorhiza palmata (Columbo) Root 6X
Rosmarinus officinalis (Rosemary) Leaf 6X
Stibium metallicum (Antimony) 15X
Thymus vulgaris Aerial Parts 6X
Valeriana officinalis (Valerian) Root 6X

Uses
For the temporary relief of symptoms associated with dizziness, mental fatigue and nervousness.

Warnings
Stop use and ask a doctor if symptoms persist or worsen.
If pregnant or breastfeeding, ask a health professional before use.
Keep out of reach of children.
In case of overdose, get medical help or contact a Poison Control Center right away.

Stop use and ask a doctor if symptoms persist or worsen.

PREGNANCY OR BREAST FEEDING

If pregnant or breastfeeding, ask a health professional before use.

Keep out of reach of children.

OVERDOSAGE

In case of overdose, get medical help or contact a Poison Control Center right away.

Inactive ingredients
Ethanol (beet), purified water

Other information
Do not use if seal is missing or broken.
Store in a cool, dry place.

Directions
Adults and adolescents (12 years and older): Take 5 drops three times daily or as
recommended by your healthcare practitioner.
Children (under 12 years): Take under the direction of your
healthcare practitioner.

INDICATIONS AND USAGE

UsesUses
For the temporary relief of symptoms associated with dizziness, mental fatigue and nervousness.

Directions
Adults and adolescents (12 years and older): Take 5 drops three times daily or as
recommended by your healthcare practitioner.
Children (under 12 years): Take under the direction of your
healthcare practitioner.

Active ingredients

Each drop contains:

Aluminium metallicum (Aluminum) 12X
Asperula odorata (Sweet woodruff) Aerial Parts 4X
Equisetum arvense (Common horsetail) Stem 4X
Jateorhiza palmata (Columbo) Root 4X
Marrubium vulgare (Common horehound) Aerial Parts 4X
Ocimum basilicum Aerial Parts 4X
Stannum metallicum (Tin) 12X

Uses

For the temporary relief of symptoms associated with poor digestion.

Warnings
Stop use and ask a doctor if symptoms persist or worsen.
If pregnant or breastfeeding, ask a health professional before use.
Keep out of reach of children.
In case of overdose, get medical help or contact a Poison Control Center right away.

Stop use and ask a doctor if symptoms persist or worsen.

PREGNANCY OR BREAST FEEDING

If pregnant or breastfeeding, ask a health professional before use.

Keep out of reach of children.

OVERDOSAGE

In case of overdose, get medical help or contact a Poison Control Center right away.

Inactive ingredients
Ethanol (beet), purified water

Other information
Do not use if seal is missing or broken.
Store in a cool, dry place.

Directions
Adults and adolescents (12 years and older): Take 5 drops three times daily or as
recommended by your healthcare practitioner.
Children (under 12 years): Take under the direction of your
healthcare practitioner.

Uses

For the temporary relief of symptoms associated with poor digestion.

Directions
Adults and adolescents (12 years and older): Take 5 drops three times daily or as
recommended by your healthcare practitioner.
Children (under 12 years): Take under the direction of your
healthcare practitioner.

PACKAGE LABEL

NDC 62106-1146-8

UNDA

numbered compounds
UNDA 47
Homeopathic Preparation

For the temporary relief of symptoms
associated with dizziness, mental
fatigue and nervousness.
Contains 31% Alcohol
0.7 fl oz (20 ml)

PACKAGE LABEL

NDC 62106-1142-8

UNDA
numbered compounds
UNDA 43
Homeopathic Preparation

For the temporary relief of symptoms
associated with poor digestion.
Contains 31% Alcohol
0.7 fl oz (20 ml)